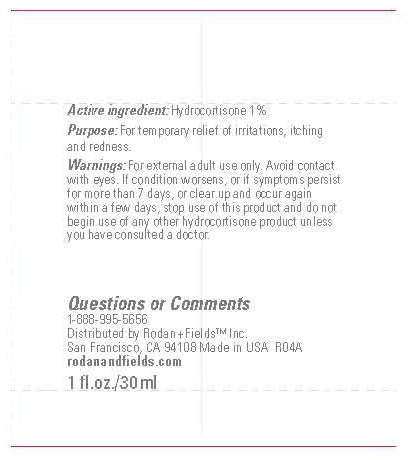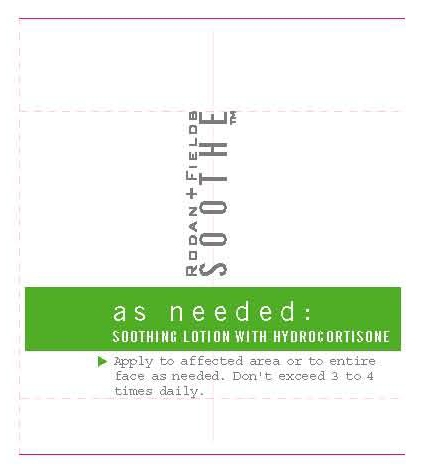 DRUG LABEL: Rodan and Fields
NDC: 56152-2003 | Form: CREAM
Manufacturer: Cosmetic Enterprises Ltd.
Category: otc | Type: HUMAN OTC DRUG LABEL
Date: 20100706

ACTIVE INGREDIENTS: HYDROCORTISONE 1 mg/100 mL

Soothe

Active Ingredients

Hydrocortisone 1%

WARNINGS

Warnings: for external adult use only. Avoid contact with eyes. If condition worsens, or if symptoms persist for more than 7 days, or clear up and occur again within a few days, stop use of this product and do not begin use of any other hydrocortisone product unless you have consulted a doctor.

INDICATIONS AND USAGE

Purpose: for temporary relief of irritations, itching and redness.

Questions or Comments
1-888-995-5656

PACKAGE LABEL

Soothe

Soothing lotion with hydrocortisone

1 fl. oz./30 mL